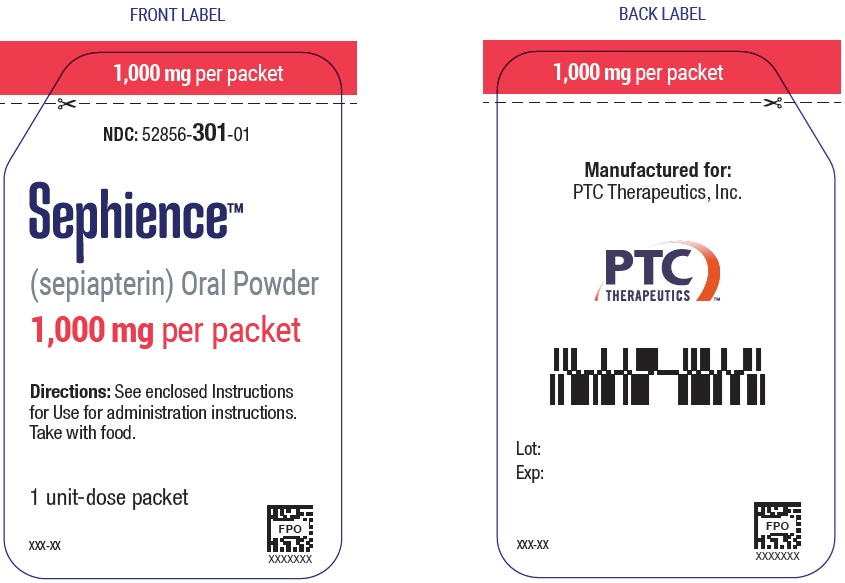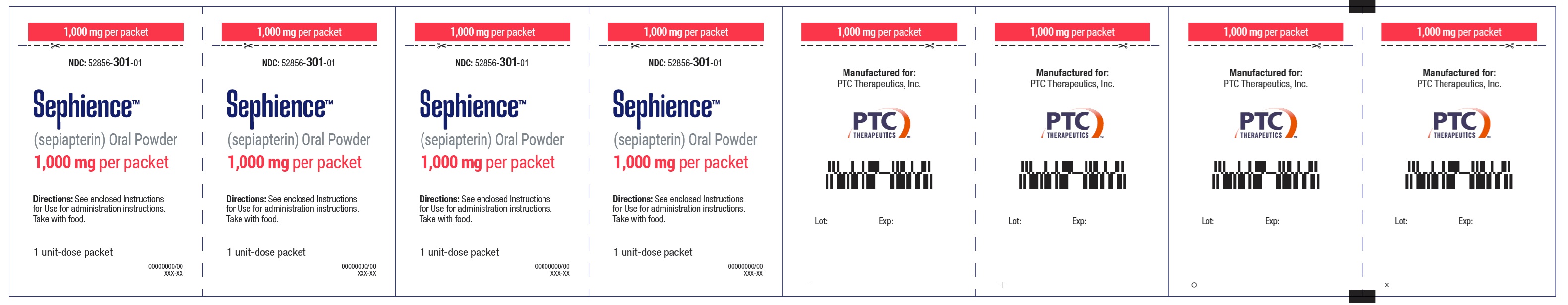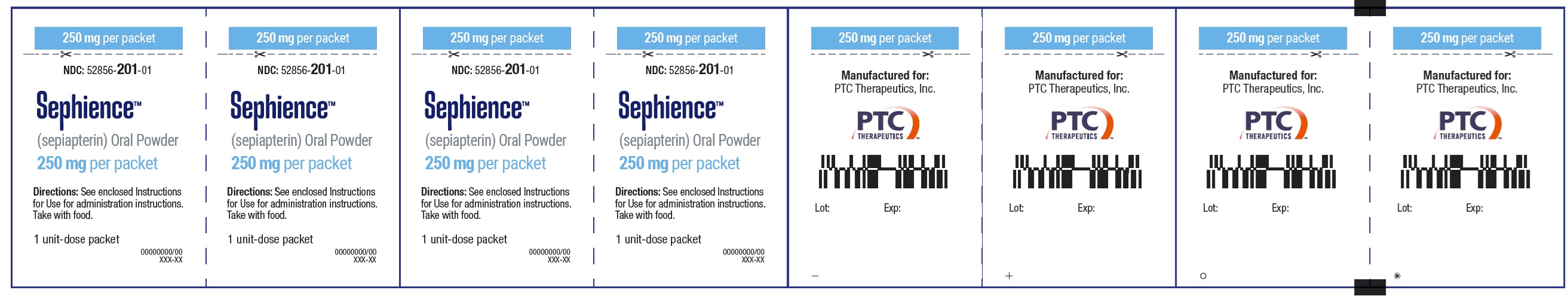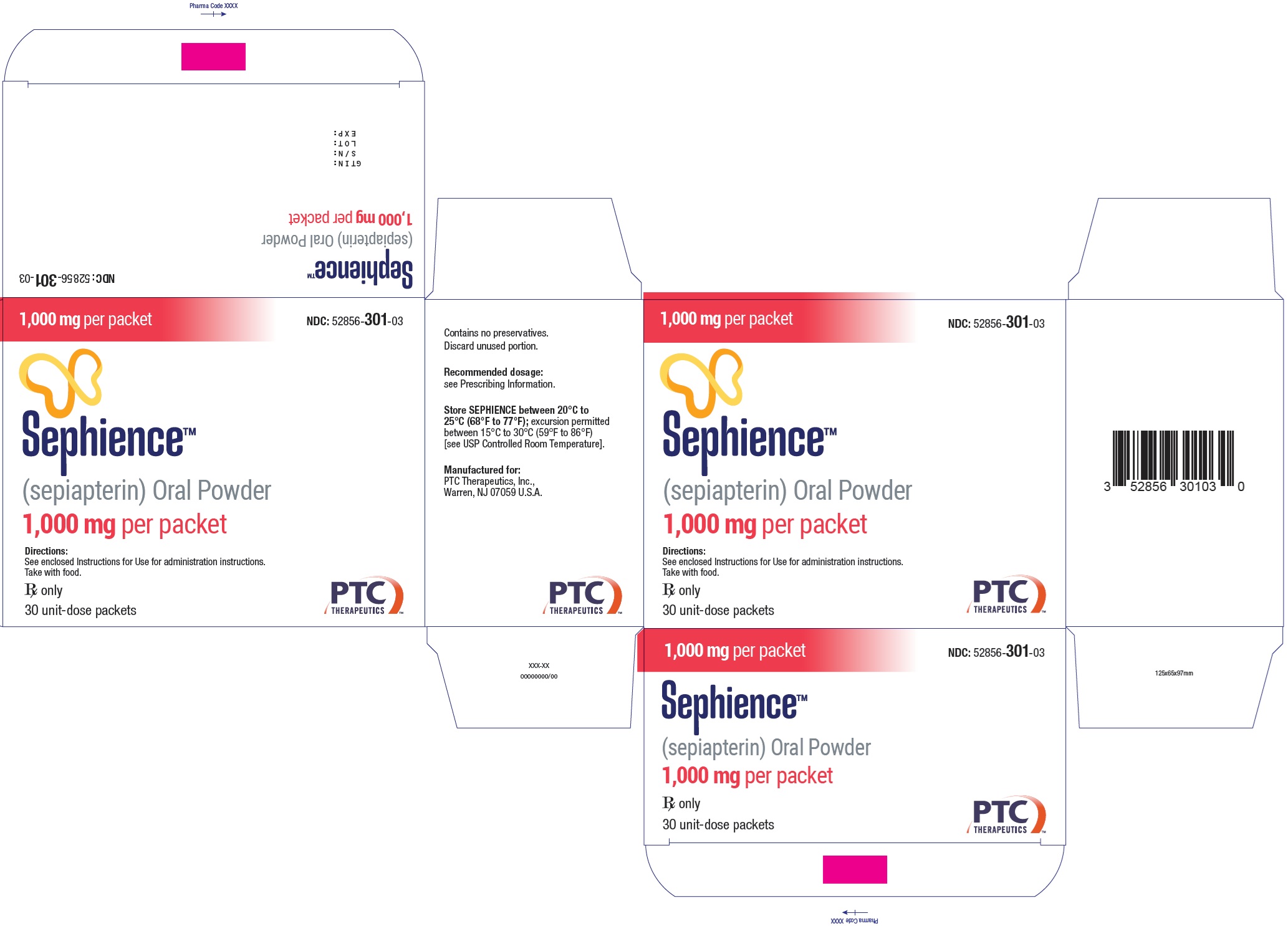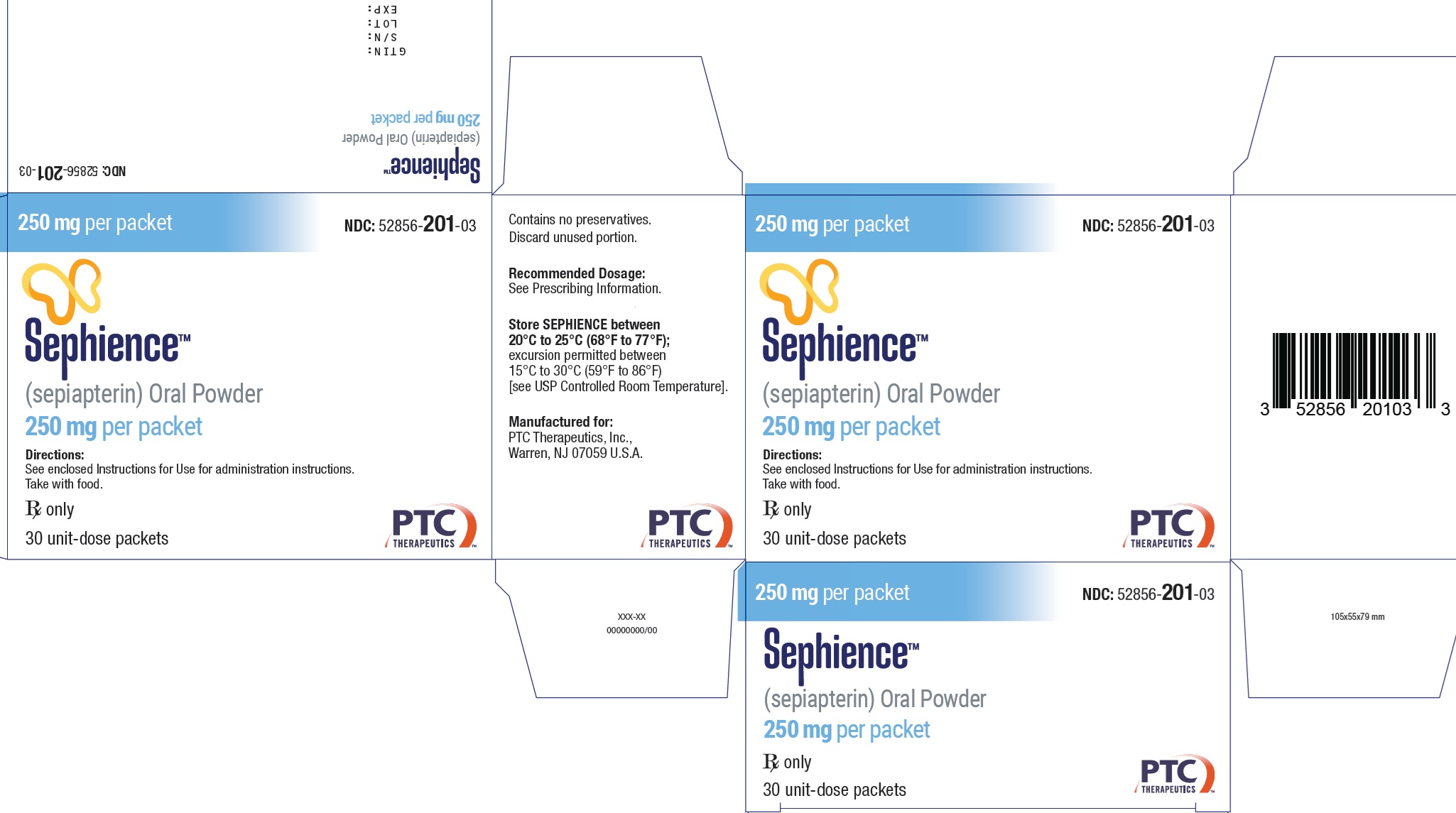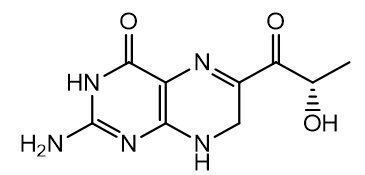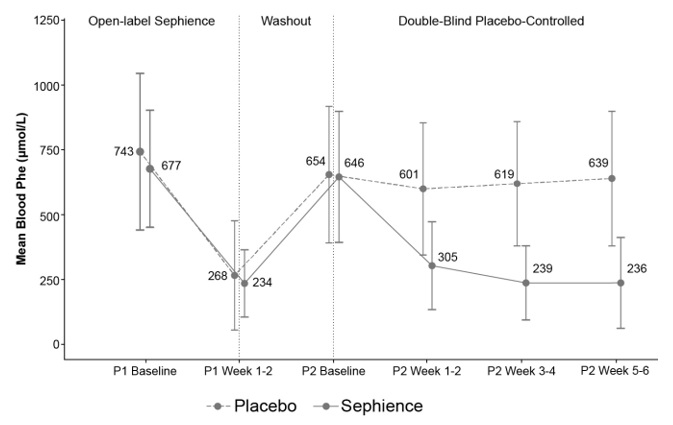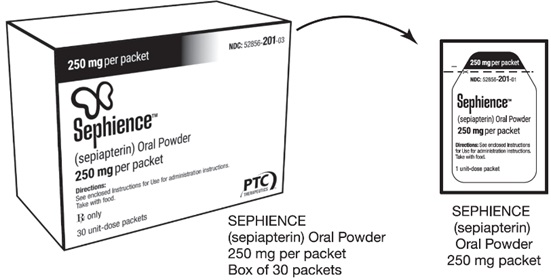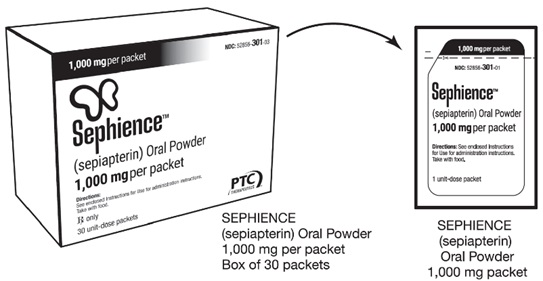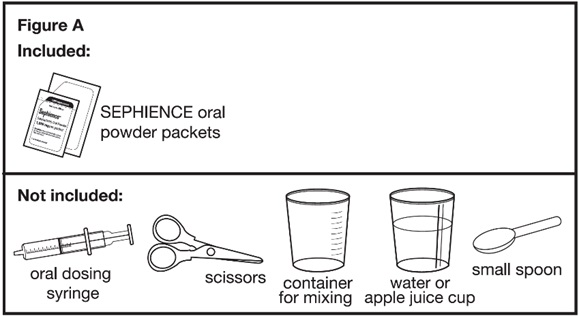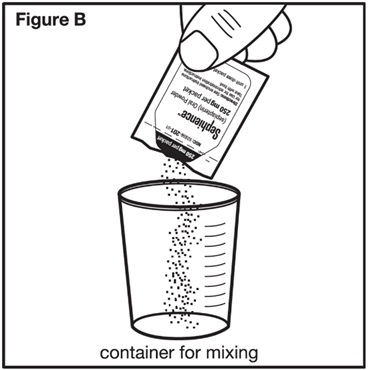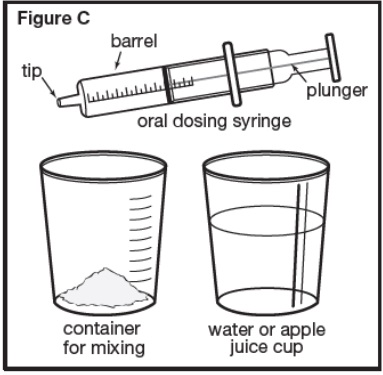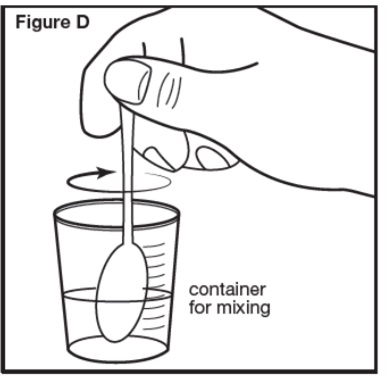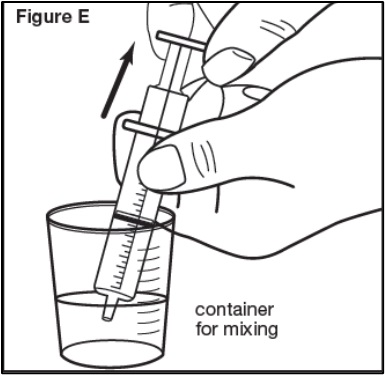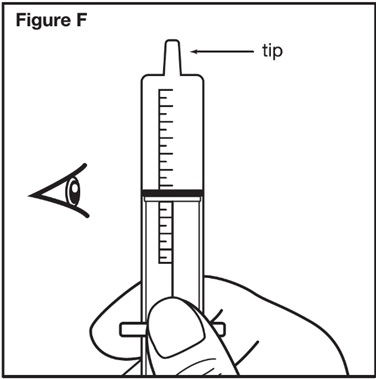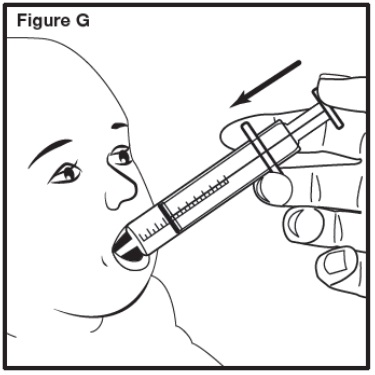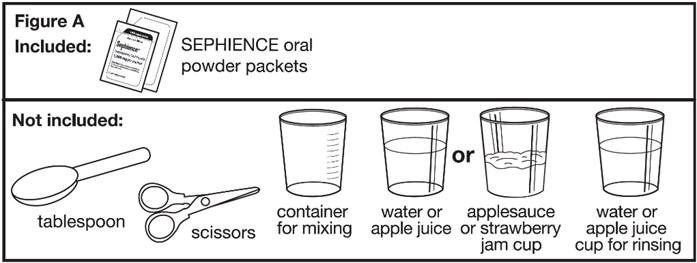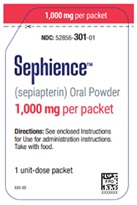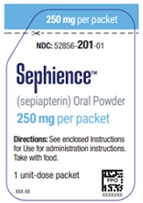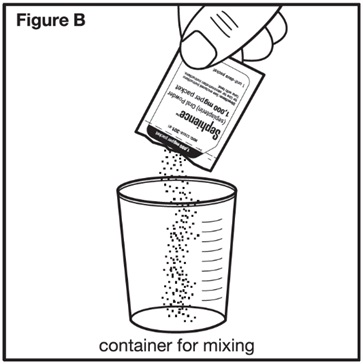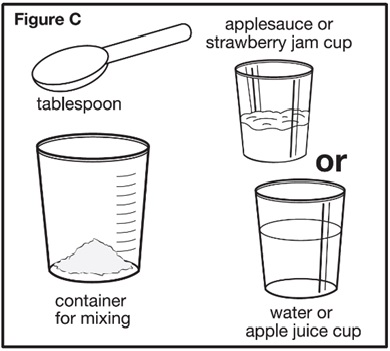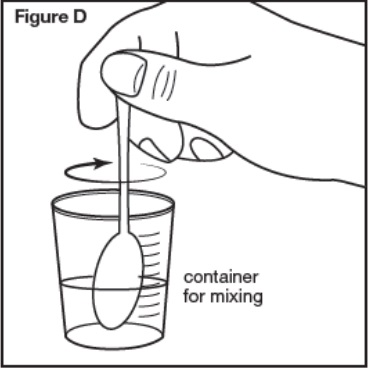 DRUG LABEL: Sephience
NDC: 60468-006 | Form: POWDER
Manufacturer: allphamed Pharbil Arzneimittel GmbH
Category: prescription | Type: HUMAN PRESCRIPTION DRUG LABEL
Date: 20251002

ACTIVE INGREDIENTS: SEPIAPTERIN 1000 mg/1 1
INACTIVE INGREDIENTS: SILICON DIOXIDE; CROSCARMELLOSE SODIUM; ISOMALT; MAGNESIUM STEARATE; MANNITOL; MICROCRYSTALLINE CELLULOSE; SUCRALOSE; XANTHAN GUM

HIGHLIGHTS OF PRESCRIBING INFORMATION

These highlights do not include all the information needed to use SEPHIENCE safely and effectively. See full prescribing information for SEPHIENCE.
SEPHIENCE (sepiapterin) oral powder
Initial U.S. Approval: 2025

1 INDICATIONS AND USAGE

SEPHIENCE is a phenylalanine hydroxylase (PAH) activator indicated for the treatment of hyperphenylalaninemia (HPA) in adult and pediatric patients 1 month of age and older with sepiapterin-responsive phenylketonuria (PKU). SEPHIENCE is to be used in conjunction with a phenylalanine (Phe)- restricted diet. (1)

2 DOSAGE AND ADMINISTRATION

- Patients treated with SEPHIENCE should be on a dietary protein and a Phe-restricted diet. (2.1)
- Administer SEPHIENCE orally once daily with food. (2.2)
- The recommended starting dosage of SEPHIENCE is: (2.2)
  Age | SEPHIENCE (mg/kg) per day
  Less than 6 months | 7.5 mg/kg
  6 months to less than 1 year | 15 mg/kg
  1 year to less than 2 years | 30 mg/kg
  2 years and older | 60 mg/kg
- Important Administration Information: prepare SEPHIENCE calculated daily doses of < 1,000 mg as a liquid mixture (25 mg/mL), and administer exact prescribed dose volume (mL). (2.2, 2.3)
- See full prescribing information for complete preparation and administration instructions. (2.3)

3 DOSAGE FORMS AND STRENGTHS

Oral Powder: 250 mg (3)

Oral Powder: 1000 mg (3)

4 CONTRAINDICATIONS

None. (4)

5 WARNINGS AND PRECAUTIONS

- Increased Bleeding: SEPHIENCE may increase the risk of bleeding. Consider treatment interruption in patients with active bleeding. (5.1)
- Hypophenylalaninemia: Some pediatric PKU patients experienced hypophenylalaninemia; monitor patients blood Phe levels during treatment. (5.2)
- Interaction with Levodopa: Seizures, over-stimulation or irritability may occur; monitor patients for a change in neurologic status. (5.3)

6 ADVERSE REACTIONS

Most common adverse reactions with SEPHIENCE (≥2% and greater than placebo) were diarrhea, headache, abdominal pain, hypophenylalaninemia, feces discoloration, and oropharyngeal pain. (6.1)

To report SUSPECTED ADVERSE REACTIONS, contact PTC Therapeutics, Inc. at 1-866-562-4620 or FDA at 1-800-FDA-1088 or www.fda.gov/medwatch.

7 DRUG INTERACTIONS

Dihydrofolate Reductase (DHFR) Inhibitors: Avoid concomitant use (e.g., trimethoprim, methotrexate, trimetrexate, pemetrexed, pralatrexate, raltitrexed, or piritrexim). (7.1)

Sepiapterin Reductase (SR) Inhibitors: Avoid concomitant use (e.g. sulfasalazine or sulfamethoxazole). (7.1)

Interaction with Levodopa: Monitor patients for a change in neurologic status. (7.2)

Drugs Affecting Nitric Oxide-Mediated Vasorelaxation: Potential for vasorelaxation; monitor blood pressure (e.g., PDE-5 inhibitors). (7.2)

FULL PRESCRIBING INFORMATION

1 INDICATIONS AND USAGE

SEPHIENCE is indicated for the treatment of hyperphenylalaninemia (HPA) in adult and pediatric patients 1 month of age and older with sepiapterin-responsive phenylketonuria (PKU). SEPHIENCE is to be used in conjunction with a phenylalanine (Phe)-restricted diet.

2 DOSAGE AND ADMINISTRATION

2.1 Important Recommendation Prior to SEPHIENCE Treatment

Treatment with SEPHIENCE should be directed by physicians knowledgeable in the management of PKU.

Biochemical response to SEPHIENCE treatment cannot generally be pre-determined by laboratory testing (e.g., molecular testing), and should be determined through a therapeutic evaluation of SEPHIENCE [see Dosage and Administration (2.2) and Clinical Studies (14.1)].

Obtain baseline blood Phe concentration before initiating treatment.

All patients with PKU who are treated with SEPHIENCE should be on a dietary protein and Phe-restricted diet that is based on blood Phe levels. Patients should undergo regular dietary assessments, including protein and Phe intake, by their healthcare provider [see Dosage and Administration (2.2)].

2.2 Recommended Dosage and Administration

The recommended starting dosage of SEPHIENCE is based on the patient’s age and is administered orally once daily (see Table 1).

Administer SEPHIENCE with food [see Clinical Pharmacology (12.3)] .

Table 1: Recommended Starting Dosage of SEPHIENCE*in Pediatric and Adult Patients
Age | SEPHIENCE (mg/kg) per day**
Less than 6 months | 7.5 mg/kg
6 months to less than 1 year | 15 mg/kg
1 year to less than 2 years | 30 mg/kg
2 years and older | 60 mg/kg
*For calculated daily doses less than 1,000 mg, the final concentration of prepared SEPHIENCE liquid mixture is 25 mg/mL [see Dosage and Administration (2.3)] .
**60 mg/kg is the maximum daily dose for all patients.

Evaluation Period

Dosage Titration in Patients Less than 2 Years of Age

After initiating treatment at the starting dosage by age (Table 1), check blood Phe levels to determine response to treatment within 2 weeks. If blood Phe does not decrease, SEPHIENCE dosage may be titrated incrementally based on blood Phe levels to a maximum daily dosage of 60 mg/kg. Existing dietary protein and Phe intake should not be modified during the evaluation period.

Discontinuation for Lack of Biochemical Response

Discontinue SEPHIENCE in patients whose blood Phe does not decrease after 2 weeks of treatment at the maximum daily dosage of 60 mg/kg.

Dosage Modification and Monitoring

Monitor blood Phe levels during treatment, and if needed, modify the daily dosage of SEPHIENCE within the range of 7.5 mg/kg to 60 mg/kg and/or dietary protein and Phe intake to ensure adequate blood Phe level control. Frequent blood Phe monitoring is recommended in the pediatric population [see Warnings and Precautions (5.2)] .

Missed Dose

A missed dose should be taken as soon as possible but 2 doses should not be administered on the same day. Resume the normal dosing schedule the following day.

2.3 Preparation and Administration Instructions

Doses Less Than 1,000 mg (administration based on 25 mg/mL concentration)

- Determine the required number of SEPHIENCE packets and the required volume of water or apple juice to achieve a concentration of 25 mg/mL mixture (see Table 2).

Table 2: Number of SEPHIENCE Packets and Volume to Prepare a SEPHIENCE Mixture of 25 mg/mL for Doses Less than 1,000 mg
Daily Dose (mg) | Number of 1,000 mg packetsa | Number of 250 mg packetsa | Volume of water or apple juice (mL)
250 mg or less | 0 | 1 | 9 mL
251 mg to 500 mg | 0 | 2 | 18 mL
501 mg to 750 mg | 0 | 3 | 27 mL
751 mg to 999 mg | 1 | 0 | 36 mL
Abbreviations: mg, milligrams; mL, milliliters
aFor calculated daily doses less than 1,000 mg, round the dose up to the nearest 250 mg to determine the number of SEPHIENCE packets and prepare each 250 mg packet with 9 mL of water or apple juice.

- Calculate the prescribed dose volume to the nearest 0.2 mL.
  - Divide the calculated daily dose (mg) by the final concentration (25 mg/mL) of SEPHIENCE liquid mixture for doses less than 1,000 mg.
    Prescribed dose volume (mL)= SEPHIENCE calculated dose (mg))
    25 mg/mL
- Prepare a liquid mixture.
  - Open and empty the entire content of each SEPHIENCE packet into an appropriate-size container and mix with the required volume of water or apple juice per Table 2.
  - Stir the contents for 30 seconds or more until the mixture is uniformly mixed.
  - Using a graduated oral dosing syringe, draw up the prescribed dose volume to the nearest 0.2 mL.
- Administer the prescribed dose volume (mL).
  - Administer immediately.
  - If particles are remaining in the syringe, draw up additional water or apple juice and administer the contents immediately. Repeat if particles still remain.
  - Discard unused portion of SEPHIENCE mixture remaining in the container.
  - Consume additional food after administration of the prescribed dose volume.

Doses 1,000 mg or Greater (whole packet administration)

- Determine the required number of SEPHIENCE packets and the required volume of water, apple juice, strawberry jam, or applesauce (see Table 3).

Table 3: Number of SEPHIENCE Packets and Volume to Prepare a SEPHIENCE Mixture for Doses of 1,000 mg or Greater
Daily Dose (mg) | Number of 1,000 mg packetsa | Number of 250 mg packetsa | Volume of water, apple juice, strawberry jam, or applesauceb
1,000 mg to 1,124 mg | 1 | 0 | 2 Tbsp or 30 mL
1,125 mg to 1,374 mg | 1 | 1 | 4 Tbsp or 60 mL
1,375 mg to 1,624 mg | 1 | 2 | 4 Tbsp or 60 mL
1,625 mg to 1,874 mg | 1 | 3 | 4 Tbsp or 60 mL
1,875 mg to 2,124 mg | 2 | 0 | 4 Tbsp or 60 mL
2,125 mg to 2,374 mg | 2 | 1 | 6 Tbsp or 90 mL
2,375 mg to 2,624 mg | 2 | 2 | 6 Tbsp or 90 mL
2,625 mg to 2,874 mg | 2 | 3 | 6 Tbsp or 90 mL
2,875 mg to 3,124 mg | 3 | 0 | 6 Tbsp or 90 mL
3,125 mg to 3,374 mg | 3 | 1 | 8 Tbsp or 120 mL
3,375 mg to 3,624 mg | 3 | 2 | 8 Tbsp or 120 mL
3,625 mg to 3,874 mg | 3 | 3 | 8 Tbsp or 120 mL
3,875 mg to 4,124 mg | 4 | 0 | 8 Tbsp or 120 mL
4,125 mg to 4,374 mg | 4 | 1 | 10 Tbsp or 150 mL
4,375 mg to 4,624 mg | 4 | 2 | 10 Tbsp or 150 mL
4,625 mg to 4,874 mg | 4 | 3 | 10 Tbsp or 150 mL
4,875 mg to 5,124 mg | 5 | 0 | 10 Tbsp or 150 mL
5,125 mg to 5,374 mg | 5 | 1 | 12 Tbsp or 180 mL
5,375 mg to 5,624 mg | 5 | 2 | 12 Tbsp or 180 mL
5,625 mg to 5,874 mg | 5 | 3 | 12 Tbsp or 180 mL
5,875 mg to 6,124 mg | 6 | 0 | 12 Tbsp or 180 mL
Abbreviations: mg, milligrams; mL, milliliters; Tbsp, tablespoons
aFor calculated daily doses 1,000 mg or greater, round the dose to the nearest 250 mg to determine the number of SEPHIENCE packets required.
bFor each 1,000 mg packet, add 2 Tbsp (30 mL) of water, apple juice, strawberry jam, or applesauce, and then add an additional quantity of 2 Tbsp (30 mL) for up to three 250 mg packet(s) and then mix.

- Prepare a liquid or soft food mixture.
  - Open and empty the entire content of each SEPHIENCE packet into a container.
  - Mix with the required amount of water, apple juice, strawberry jam, or applesauce per Table 3.
  - Stir the contents for 30 seconds or more when mixing SEPHIENCE with water or apple juice or 60 seconds or more when mixing SEPHIENCE with strawberry jam or applesauce until the mixture is uniform.
- Administer the dose.
  - Consume the entire mixture immediately.
  - If particles are remaining in the container, add additional water or juice to the container and administer the contents immediately. Repeat if particles still remain.
  - Consume additional food after administration of the entire mixture.

2.4 Storage Instructions for the Liquid and Soft Food Mixtures

- If the SEPHIENCE liquid or soft food mixture is not administered immediately, cover and store the mixture at controlled room temperature between 20°C to 25°C (68°F to 77°F) for up to 6 hours or refrigerate between 2°C to 8°C (36°F to 46°F) for up to 24 hours.
- If the liquid or soft food mixture is stored, stir for at least 30 or 60 seconds, respectively, prior to administration of the prescribed dose.
- Discard unused SEPHIENCE mixture after 6 hours at controlled room temperature or after 24 hours if refrigerated.

3 DOSAGE FORMS AND STRENGTHS

Oral powder: 250 mg or 1,000 mg sepiapterin as yellow to orange powder in a unit-dose packet.

4 CONTRAINDICATIONS

None.

5 WARNINGS AND PRECAUTIONS

5.1 Increased Bleeding

SEPHIENCE may increase the risk of bleeding. Bleeding events, including superficial hematomas, prolonged bleeding, and heavy menstrual bleeding have occurred in patients treated with SEPHIENCE [see Adverse Reactions (6.1)] . One patient with non-traumatic superficial hematomas and prolonged bleeding was re-challenged at a lower dose of SEPHIENCE with recurrence of symptoms, which led to treatment discontinuation. The patient experienced symptoms 15 days after initial exposure and two days after rechallenge. The patient had normal blood counts and coagulation studies at the time of the bleeding. Inform the patient about the increased risk of bleeding associated with SEPHIENCE and to follow up with his/her healthcare provider if he/she experiences any signs of increased bleeding. Consider treatment interruption with SEPHIENCE in patients with active bleeding.

5.2 Hypophenylalaninemia

In clinical trials of SEPHIENCE, some pediatric PKU patients experienced hypophenylalaninemia (low blood Phe), including some patients with multiple low blood Phe levels, during treatment with SEPHIENCE [see Adverse Reactions (6.1)] . Prolonged levels of blood Phe that are too low have been associated with catabolism and endogenous protein breakdown, which has been associated with adverse developmental outcomes.

Monitor blood Phe levels during treatment and if needed, modify the dosage of SEPHIENCE and/or dietary protein and Phe intake to ensure adequate blood Phe level control. Frequent blood Phe monitoring is recommended in the pediatric population [see Dosage and Administration (2.2)] .

5.3 Interaction with Levodopa

In a 10-year post-marketing safety surveillance program for a non-PKU indication using another drug that is a phenylalanine hydroxylase (PAH) activator, 3 patients with underlying neurological disorders experienced seizures, exacerbation of seizures, over-stimulation, and irritability during co-administration with levodopa. Monitor patients who are receiving levodopa for changes in neurological status during treatment with SEPHIENCE [see Drug Interactions (7.2)] .

6 ADVERSE REACTIONS

The following clinically significant adverse reactions are described elsewhere in the labeling:

- Increased Bleeding [see Warnings and Precautions (5.1)] .
- Hypophenylalaninemia [see Warnings and Precautions (5.2)] .

6.1 Clinical Trials Experience

Because clinical trials are conducted under widely varying conditions, adverse reaction rates observed in the clinical trials of a drug cannot be directly compared to rates in the clinical trials of another drug and may not reflect the rates observed in practice.

The safety of SEPHIENCE was evaluated in Trial 1 [Part 1 (open label); Part 2, (placebo-controlled)]; and Trial 2 (open-label). The two trials included a total of 215 SEPHIENCE-treated patients with PKU: 10 (5%) were <2 years old, 118 (55%) were ≥2 and <17 years old, and 87 (40%) were ≥17 years old. All patients received SEPHIENCE from 7.5 mg/kg/day up to 60 mg/kg/day and the median duration of treatment (in weeks) was 25.5 [see Clinical Studies (14.1)] .

Trial 1

Trial 1 included a total of 157 patients (85 male and 72 female, aged 1 year to 61 years old) with PKU across both parts of the trial. The patients received dosages from 20 mg/kg up to 60 mg/kg daily and the median duration of treatment was 8 weeks.

Table 4lists the most common adverse reactions that were reported in ≥2% of patients treated with SEPHIENCE and greater than that of the placebo group in Part 2 of Trial 1.

Table 4: Adverse Reactions for SEPHIENCE in Adult and Pediatric Patients with PKU that Occurred in ≥2% of Sepiapterin-Treated Patients and Greater than Placebo (Trial 1 Part 2)
Adverse Reaction | SEPHIENCE N=56 N (%) | Placebo N=54 N (%)
Diarrhea | 4 (7) | 1 (2)
Headache | 4 (7) | 1 (2)
Abdominal paina | 3 (5) | 1 (2)
Hypophenylalaninemia | 2 (4) | 0
Feces discoloration | 2 (4) | 0
Oropharyngeal pain | 2 (4) | 1 (2)
aIncludes Abdominal pain; Abdominal pain upper, Abdominal discomfort.

Adverse reactions were similar across both adult and pediatric populations except for hypophenylalaninemia (see Description of Selected Adverse Reactions).

Description of Selected Adverse Reactions

Increased Bleeding

In Trial 1 Part 2, a case of heavy menstrual bleeding was reported in a SEPHIENCE-treated patient. Less than 2% of patients in Trial 2 experienced increased bleeding, which included heavy menstrual bleeding, non-traumatic superficial hematomas, and prolonged bleeding.

Hypophenylalaninemia

In Trial 1 Part 2, hypophenylalaninemia was seen in 5% (2/37) of sepiapterin-treated pediatric patients and in no adult patients. Some pediatric patients in Trial 2 had multiple low blood Phe levels.

7 DRUG INTERACTIONS

7.1 Effects of Other Drugs on SEPHIENCE

Avoid concomitant use of drugs known to inhibit folate synthesis dihydrofolate reductase (DHFR) (e.g., trimethoprim, methotrexate, trimetrexate, pemetrexed, pralatrexate, raltitrexed, and piritrexim) while taking SEPHIENCE. Concomitant administration of such drugs may reduce sepiapterin metabolism to tetrahydrobiopterin (BH4). If concomitant use is not avoidable, monitor blood Phe levels.

Avoid concomitant use of sepiapterin reductase (SR) inhibitors with SEPHIENCE. Concomitant administration of such drugs may reduce sepiapterin metabolism to BH4. If concomitant use is not avoidable, monitor blood Phe levels.

7.2 Effects of SEPHIENCE on Other Drugs

SEPHIENCE may increase the availability of tyrosine, a precursor of levodopa. Neurologic events were reported postmarketing in patients receiving another PAH activator and levodopa concomitantly for a non-PKU indication. Monitor patients for a change in neurologic status when levodopa is administered with SEPHIENCE [see Warnings and Precautions (5.3)] .

7.3 Drugs Affecting Nitric Oxide-Mediated Vasorelaxation

SEPHIENCE and PDE-5 inhibitors induce vasorelaxation, thus concomitant use of SEPHIENCE with PDE-5 inhibitors may reduce blood pressure even further. Monitor for signs and symptoms of hypotension with concomitant use of SEPHIENCE with drugs that affect nitric oxide-mediated vasorelaxation (e.g., PDE-5 inhibitors such as sildenafil, vardenafil, or tadalafil).

8 USE IN SPECIFIC POPULATIONS

8.1 Pregnancy

Risk Summary

Available data on the use of SEPHIENCE during pregnancy are insufficient to evaluate for a drug-associated risk of major birth defects, miscarriage, or other adverse maternal or fetal outcomes. Uncontrolled blood Phe concentrations before and during pregnancy are associated with an increased risk of adverse pregnancy outcomes and fetal adverse effects (see Clinical Considerations) .

In animal reproduction studies, oral administration of sepiapterin to pregnant rats and rabbits during organogenesis at dose exposures up to 9- and 6- times the human exposure at the maximum recommended human dose (MRHD) of 60 mg/kg, respectively, resulted in no adverse developmental effects (see Data).

All pregnancies have a background risk of birth defects, loss, or other adverse outcomes. In the U.S. general population, the estimated background risk of major birth defects and miscarriage in clinically recognized pregnancies is 2% to 4% and 15% to 20%, respectively. The background risk of major birth defects and miscarriage in pregnant women with PKU who maintain blood Phe concentrations greater than 600 micromol/L during pregnancy is greater than the corresponding background risk for pregnant women without PKU.

Clinical Considerations

Disease-Associated Maternal and/or Embryofetal Risk

Uncontrolled blood Phe concentrations before and during pregnancy are associated with an increased risk of adverse outcomes and fetal adverse effects (see Data). To reduce the risk of hyperphenylalaninemia-induced fetal adverse effects, blood Phe concentrations should be maintained between 120 and 360 micromol/L during pregnancy and during the 3 months before conception [see Dosage and Administration (2.2)] .

Data

Human Data

Available data from the Maternal Phenylketonuria Collaborative Study on 468 pregnancies and 331 live births in pregnant women with PKU demonstrated that uncontrolled Phe concentrations above 600 micromol/L are associated with an increased risk for major birth defects (including microcephaly, major cardiac malformations), intrauterine fetal growth retardation, and future intellectual disability with low IQ.

Animal Data

In an embryo-fetal development study in rats, SEPHIENCE was administered at dose levels of 100, 300, or 1,000 mg/kg/day via oral gavage to pregnant rats during the period of organogenesis from gestation day (GD) 7 to GD 17. There were no maternal or embryo-fetal developmental toxicities noted at doses up to 1,000 mg/kg/day (9-fold the human AUC0-24at the MRHD).

In an embryo-fetal development study in pregnant rabbits, SEPHIENCE was administered at dose levels of 100, 300, or 1,000 mg/kg/day via oral gavage to pregnant rabbits during the period of organogenesis from gestation day (GD) 7 to GD 19. There were no maternal or embryo-fetal developmental toxicities at doses up to 1,000 mg/kg/day (6-fold the human AUC0-24at the MRHD).

In the pre- and post-natal development study in rats, SEPHIENCE was administered at dose levels of 30, 100, and 300 mg/kg/day via oral gavage once daily to pregnant rats from GD 6 to lactation day 20. SEPHIENCE did not induce effects on maternal reproductive function or on developmental and reproductive parameters of male and female offspring up to 300 mg/kg (7-fold the human AUC0-24at the MRHD).

8.2 Lactation

Risk Summary

There are no data on the presence of sepiapterin in either human or animal milk, the effects on the breastfed infant, or the effects on milk production. The developmental and health benefits of breastfeeding should be considered along with the mother’s clinical need for SEPHIENCE and any potential adverse effects on the breastfed infant from SEPHIENCE or from the underlying maternal condition.

8.4 Pediatric Use

The safety and effectiveness of SEPHIENCE have been established in pediatric patients 1 month of age and older. Use of SEPHIENCE for this indication is supported by evidence from one adequate and well-controlled trial in 63 pediatric patients with PKU aged 1 to <17 years old (Trial 1) and additional safety and efficacy information obtained from an ongoing open label trial in adult and pediatric patients with PKU (Trial 2) [see Clinical Studies (14.1)] .

In Trial 1 Part 2, hypophenylalaninemia was seen in 5.4% (2/37) of sepiapterin-treated pediatric patients and in no adult patients. Some pediatric patients in Trial 2 had multiple low blood Phe levels [see Adverse Reactions (6.1)] .

The safety and effectiveness of SEPHIENCE for treatment of PKU have not been established in pediatric patients younger than 1 month of age.

8.5 Geriatric Use

Clinical studies of SEPHIENCE did not include patients 65 years of age and older to determine if they respond differently from younger adult patients.

11 DESCRIPTION

SEPHIENCE (sepiapterin) contains the drug substance sepiapterin, a PAH activator. Sepiapterin is a yellow to orange powder. Sepiapterin is slightly soluble in water with the solubility at 1.4 mg/mL.

The chemical name of sepiapterin is (S)-2-amino-6-(2-hydroxypropanoyl)-7,8-dihydropteridin-4(3H)-one. The molecular formula is C9H11N5O3 and the molecular weight is 237.22 g/mol. The structural formula is:

SEPHIENCE oral powder contains either 250 mg or 1,000 mg of sepiapterin to be administered orally. The inactive ingredients are: colloidal silicon dioxide, croscarmellose sodium, isomalt, magnesium stearate, mannitol, microcrystalline cellulose, sucralose, and xanthan gum.

12 CLINICAL PHARMACOLOGY

12.1 Mechanism of Action

SEPHIENCE is a precursor of the enzymatic co-factor tetrahydrobiopterin (BH4) which activates PAH.

12.2 Pharmacodynamics

Cardiac Electrophysiology

At the recommended SEPHIENCE dose of 60 mg/kg orally once daily, clinically significant QTc interval prolongation was not observed.

12.3 Pharmacokinetics

Following oral administration, sepiapterin reached the maximum concentration in plasma at 2 hours post-treatment and converted to pharmacologically active metabolite BH4with the exposures of sepiapterin generally less than 2% of those of BH4(Table 5).

There was no accumulation for BH4following repeated once daily dose up to 60 mg/kg administered in adult healthy volunteers.

When administered with a high-fat, high-calorie meal in adult healthy volunteers, BH4exposures increased less than dose proportionally (with slopes 0.87 and 0.84 for Cmaxand AUC0-last, respectively) in the dose range 5 to 20 mg/kg and less than dose proportionally (with slopes 0.1957 and 0.3189 for Cmaxand AUC0-last, respectively) in the dose range 20 to 60 mg/kg.

The pharmacokinetics of sepiapterin and its active metabolite BH4following oral administration of sepiapterin at 60 mg/kg with food in adult patients with PKU are summarized in Table 5.

Table 5: Summary of Pharmacokinetic Parameters of Sepiapterin and BH4Following Oral Administration of Sepiapterin at 60 mg/kg with Foodain Adult Patients (Age ≥17 Years) with PKU
Analyte |  | Tmax(hr) Median (Range) | Cmax(ng/mL) Mean (SD) | AUCinf ng*hr/mL) Mean (SD) | AUC24 (ng*hr/mL) Mean (SD)
Sepiapterin | N Results | 29 2 (0.5, 6.1) | 29 2.9 (1.6) | NC | 27 19.9 (18.3)
BH4 | N Results | 30 4 (2, 8) | 30 432 (177) | 19 3,626 (1267) | 30 3,618 (1,699)
aSepiapterin was administered with dietary Phe restriction. NC: not calculated. Sepiapterin plasma concentration quickly declines to below lower limit of quantitation by 12 hours post dose and AUCinf were not estimable for the majority of patients.

Absorption

The time to maximum plasma concentration (Tmax) of sepiapterin is approximately 1 to 3 hours after oral administration. Plasma sepiapterin is rapidly metabolized to BH4and peak BH4concentrations are achieved approximately 4 hours after the oral administration of sepiapterin.

Effect of Food

Administration of SEPHIENCE with food results in increased exposure to sepiapterin and BH4. When SEPHIENCE was administered at 20 or 60 mg/kg daily with a low-fat meal in healthy adult subjects, BH4exposures were 169% to 172% higher for Cmaxand 162% to 173% higher for AUC0-24hcompared to administration under fasted conditions. When sepiapterin at 20 or 60 mg/kg was administered with a high-fat, high-calorie meal, BH4exposures were 221% to 226% higher for Cmaxand 251% to 284% higher for AUC0-24hcompared to administration under fasted conditions [see Dosage and Administration (2.2)] .

Distribution

Sepiapterin mean human plasma protein binding was 15.4% in the presence of 0.1% dithiothreitol (DTT) in the concentration range of 0.1 to 10 μM. BH4mean human plasma protein binding was between 24.1% and 41.3% in the concentration range 2 to 15 μM in the presence of 0.5% β-mercaptoethanol. Sepiapterin apparent volume of distribution could not be estimated reliably as sepiapterin is converted to BH4post oral administration and plasma concentration declines to below lower limit of quantitation generally by 12 hours postdose. BH4apparent volume of distribution is 11433 (5790) L in adult patients with PKU. Increase of BH4in cerebrospinal fluid was detected after oral administration of sepiapterin 60 mg/kg QD for 7 days in healthy adult subjects.

Elimination

Following oral administration, sepiapterin is quickly absorbed and converted to BH4. Sepiapterin plasma concentration is remarkably lower than BH4and declines rapidly to below the limit of quantitation generally by 12 hours post dose. The terminal half-life of BH4is approximately 5 hours and the apparent clearance is 1498 (848) L/h in adult patients with PKU.

Metabolism

Sepiapterin is metabolized by SR/carbonyl reductase (CR) and DHFR in a 2-step unidirectional process to form pharmacologically active metabolite BH4. BH4is further metabolized non-enzymatically or enzymatically mediated by aromatic amino acid hydroxylases, such as PAH, tyrosine hydroxylase (TH), tryptophan hydroxylase (TPH), pterin-4α-carbinolamine dehydratase (PCD), dihydropteridine reductase (DHPR), xanthine oxidase (XO), and nitric oxide synthase (NOS) in various tissues.

Extensive metabolism of sepiapterin was observed in humans following a single oral dose of^14C-sepiapterin. Absorbed sepiapterin was converted to the active metabolite BH4, with Cmaxand AUC0-24hof sepiapterin generally less than 2% of those of BH4.

Excretion

Following a single oral dose of radiolabeled sepiapterin 4,000 mg to healthy adult subjects, a mean of 6.7% was recovered in urine and 26.2% recovered in feces with a combined total recovery of 32.9% by 240 hours. The low total mass recovery is likely due to formation of volatile metabolites in human intestine. Sepiapterin was a minor component in urine and was one of the prominent radioactive components in feces.

Specific Populations

No clinically significant difference in pharmacokinetics of sepiapterin were observed based on age (range 0.5 to 61 years), sex (female 52%, male 48%), race/ethnicity (White 74%, Asian 16%, Other or not specified 7%, or American Indian or Alaska Native 3%) or ABCG2 genotype (BCRP p.Gln141Lys). The effect of renal impairment, hepatic impairment, or pregnancy on pharmacokinetics of sepiapterin or BH4is unknown.

Pediatric Patients

The pharmacokinetics of sepiapterin and BH4following oral administration of sepiapterin at 60 mg/kg with food in PKU patients ≥2 years old are summarized in Table 6.

Table 6: Summary of Pharmacokinetic Parameters of Sepiapterin and BH4Following Oral Administration of Sepiapterin at 60 mg/kg with Foodain Pediatric Patients ≥2 Years Old with PKU
Analyte |  | Tmax(hr) Median (Range) | Cmax(ng/mL) Mean (SD) | AUCinf ng*hr/mL) Mean (SD) | AUC24 (ng*hr/mL) Mean (SD)
Sepiapterin | N Results | 19 1.05 (0.5, 4) | 19 2.5 (2.1) | NA NA | 18 13.8 (15.1)
BH4 | N Results | 21 4 (1.9, 8) | 21 350 (191.9) | 16 3,466 (1,792) | 21 3,023 (1,637)
aSepiapterin was administered with dietary Phe restriction.

The pharmacokinetics of sepiapterin have not been evaluated in pediatric patients younger than 2 years of age.

Drug Interaction Studies

Both sepiapterin and BH4were a substrate and inhibitor of efflux transporter breast cancer resistance protein (BCRP) in vitro.

Oral coadministration of curcumin, a BCRP inhibitor, and sepiapterin in healthy adult subjects resulted in increases in mean AUCs and Cmaxof BH4by approximately 20% to 24%, after a single dose.

In healthy adult subjects, oral coadministration of sepiapterin and rosuvastatin, a BCRP substrate, had no impact on rosuvastatin exposures.

The pharmacokinetics of sepiapterin and BH4following sepiapterin oral administration may be affected by inhibitors of SR and/or DHFR [see Drug Interactions (7.1)] .

Sepiapterin may increase the availability of tyrosine, a precursor of levodopa [see Drug Interactions (7.2)] .

13 NONCLINICAL TOXICOLOGY

13.1 Carcinogenesis, Mutagenesis, Impairment of Fertility

Carcinogenesis

In a 6-month carcinogenicity study in Tg.rasH2 mice, sepiapterin did not increase the incidence of tumors in male or female transgenic mice at approximately 12- and 16-fold, respectively, the human exposure (AUC0-24h) at the MRHD.

Mutagenesis

Based on the weight of evidence, SEPHIENCE is not genotoxic. SEPHIENCE was negative in the Ames assay. SEPHIENCE was positive in an in vitrochromosomal aberration assay without metabolic activation but not with metabolic activation. SEPHIENCE was negative in the in vivo(micronucleus and comet) assays in rats.

Impairment of Fertility

SEPHIENCE was found to have no effect on fertility and reproductive function of male and female rats when given prior to and throughout mating in male and female rats and continuing to gestation day (GD) 7 in females at oral doses up to 300 mg/kg/day (approximately 7.5-fold the plasma exposure (AUC) at MRHD).

13.2 Animal Toxicology and/or Pharmacology

Repeated administration of SEPHIENCE in rats for 26 weeks at doses greater than 100 mg/kg/day (approximately 3-fold the plasma exposure (AUC) at MRHD) caused renal toxicity, including renal tubular degeneration associated with crystal formation. However, renal toxicity was not noted in monkeys following repeated administration of SEPHIENCE for 39 weeks up to 300 mg/kg/day (approximately 7-fold the plasma exposure (AUC) at MRHD).

14 CLINICAL STUDIES

14.1 Clinical Studies in PKU

Trial 1 (NCT05099640) was a two-part trial in adult and pediatric patients who had a diagnosis of PKU with hyperphenylalaninemia with at least 2 blood Phe measurements ≥600 μmol/L. Patients in the trial were 54% male, 90% White, 5% American Indian or Alaska Native, and 4% Other by race; 16% were identified as Hispanic or Latino. The mean age of the trial patients was 17 years (range: 1 to 61 years). At trial baseline, 8% of patients had blood Phe levels at <360 μmol/L, 36% at 360-600 μmol/L, 48% at 600-1200 μmol/L, and 8% at >1200 μmol/L.

In Part 1, 157 patients received open-label treatment with SEPHIENCE: 7.5 mg/kg orally in patients 0 to <6 months of age, 15 mg/kg in patients 6 to <12 months of age, 30 mg/kg in patients 12 months to <2 years of age, or 60 mg/kg in patients ≥2 years of age per day for 14 days. In Part 1, 66% of PKU patients showed a biochemical response to SEPHIENCE with a >30% or greater reduction in Phe level. In Part 2, after the 2-week washout period from Part 1, 98 patients aged 2 years and older who demonstrated a ≥30% reduction in blood Phe levels to SEPHIENCE treatment in Part 1 were randomized in a double-blind fashion to either SEPHIENCE 20 mg/kg daily for Weeks 1 and 2, 40 mg/kg daily for Weeks 3 and 4, 60 mg/kg daily for Weeks 5 and 6 (N=49), or placebo (N=49) for 6 weeks to assess efficacy. Twelve additional patients who had shown a 15% to 30% reduction in blood Phe during Part 1 were enrolled in Part 2 but were not included in the primary efficacy analysis.

In Part 2, the primary efficacy was assessed in patients who demonstrated a ≥30% reduction in blood Phe levels during Part 1 (N=98) by the mean change in blood Phe level from baseline to Weeks 5 and 6 in the SEPHIENCE-treated group as compared to the mean change in the placebo group, as shown in Table 7.

In Part 2 of Trial 1, 55 patients in the SEPHIENCE group and 54 patients in the placebo group completed the treatment period. One patient in the SEPHIENCE group discontinued treatment.

Table 7displays a reduction in blood Phe level from baseline to Weeks 5 and 6 in Part 2 of Trial 1 for SEPHIENCE-treated patients relative to placebo. Figure 1displays the mean blood Phe level over time by treatment group.

Table 7: Change in Blood Phe Levels from Baseline at Weeks 5 and 6 For Patients Who Had a ≥30% Reduction in Blood Phe Levels During Part 1 of Trial 1
 | SEPHIENCE (N=49) | Placebo (N=49)
Baseline Blood Phe Levela(μmol/L)
Mean (±SD) | 646.1 (253) | 654 (261.5)
Percentiles (25th, 75th) | 468.5, 769.5 | 466, 796
Weeks 5 and 6b
Mean (±SD) | 236 (174.9) | 637.9 (259.9)
Percentiles (25th, 75th) | 127.7, 291 | 453, 776
Mean Change in Blood Phe From Baseline to Weeks 5 and 6 (μmol/L)
Adjusted Mean (±SE)† | -415.8 (24.1) | -19.9 (24.2)
Percentiles (25th, 75th) | -544, -296.7 | -86.7, 63.7
Mean Percent Change in Blood Phe From Baseline to Weeks 5 and 6
Mean (±SD) | -62.8 (20.7) | 1.4 (29.2)
Percentiles (25th, 75th) | -76.9, -60.7 | -12.4, 15
Treatment difference (95% CI) in adjusted mean | -64.2 (-74.1, -54.4)
aBaseline is the average of Day -1 and Day 1 blood Phe levels in Part 2.
bBlood Phe levels were based on average values during Weeks 5 and 6.
†Adjusted mean and standard error, p-value <0.0001 for treatment difference were from a mixed model for repeated measures (MMRM) with change in blood Phe from baseline to post-baseline assessments as the response variable, and fixed effects for treatment, baseline blood Phe, baseline Phe stratum, visit and treatment-by-visit interaction.

Figure 1: Mean (±SD) Blood Phe Levels Over Time For Patients Who Had a ≥30% Reduction in Blood Phe Levels During Part 1 of Trial 1 (N=98)

Supportive efficacy data were provided from Trial 2, which is an ongoing, multicenter, open-label trial in adult and pediatric patients with a clinical diagnosis of PKU with hyperphenylalaninemia. At the data cutoff date, 169 patients, including 65 adult and 104 pediatric patients (median age: 14 years, range 2 months to 55 years) received treatment with SEPHIENCE. Five patients 2 to <6 months of age received SEPHIENCE 7.5 mg/kg, 9 patients 12 months to <2 years of age received SEPHIENCE 30 mg/kg, and 90 patients 2 to <17 years of age and 65 patients ≥17 years of age received SEPHIENCE 60 mg/kg. Of the 9 patients under the age of 2 years, 6 patients (66%) had a ≥30% decrease in blood Phe from baseline) at Weeks 1 and 2. The baseline Phe level in patients 2 years and under was 311.4 μmol/L and the mean absolute change in Phe from baseline to Weeks 1 and 2 in this age group was -125 μmol/L (standard deviation 265.9 μmol/L).

16 HOW SUPPLIED/STORAGE AND HANDLING

How Supplied

SEPHIENCE (sepiapterin) oral powder is supplied as a yellow to orange powder in a unit-dose heat-sealed laminated aluminum foil packet. Each packet contains:

250 mg sepiapterin per packet:
NDC 52856-201-03 Carton of 30-unit dose packets
NDC 52856-201-01 Single unit dose packet

1,000 mg sepiapterin per packet:
NDC 52856-301-03 Carton of 30-unit dose packets
NDC 52856-301-01 Single unit dose packet

Storage and Handling

Store SEPHIENCE at room temperature between 20°C to 25°C (68°F to 77°F); excursion permitted between 15°C to 30°C (59°F to 86°F) [see USP Controlled Room Temperature].

Store SEPHIENCE liquid or soft food mixture either refrigerated or at controlled room temperature [see Dosage and Administration (2.4)] .

17 PATIENT COUNSELING INFORMATION

Advise the patient and/or caregiver to read the FDA-approved patient labeling (Patient Information and Instructions for Use).

Increased Bleeding

Inform the patient about the increased risk of bleeding associated with SEPHIENCE and to follow up with his/her healthcare provider if he/she experiences any symptoms of increased bleeding.

Drug Interactions

Advise the patient to inform his/her healthcare provider if he/she is taking, or plan to take, any prescription or over-the-counter medications and supplements because of the potential for drug interactions [see Drug Interactions (7) and Clinical Pharmacology (12.3)] .

Feces Discoloration

Advise patients that SEPHIENCE may cause feces to have a yellow or orange discoloration.

Manufactured by
Allphamed PHARBIL Arzneimittel GmbH
Hildebrand str. 12,
37081 Gottingen,
Germany (DEU)

Manufactured for:
PTC Therapeutics, Inc.
Warren, NJ 07059

PATIENT INFORMATION

SEPHIENCE (seh-FIGH-ence)
(sepiapterin)
oral powder

What is SEPHIENCE?

SEPHIENCE is a prescription medicine used to lower blood levels of phenylalanine (Phe) in adults and children 1 month of age and older with a certain type of Phenylketonuria (PKU). SEPHIENCE is used along with a Phe-restricted diet.
It is not known if SEPHIENCE is safe and effective in children younger than 1 month of age.

Before taking or giving SEPHIENCE, tell your healthcare provider about all of your medical conditions, including if you:

- are pregnant or plan to become pregnant. It is not known if SEPHIENCE will harm your unborn baby.
- are breastfeeding or plan to breastfeed. It is not known if SEPHIENCE passes into your breast milk. Talk to your healthcare provider about the best way to feed your baby if you take SEPHIENCE.

Tell your healthcare provider about all medicines you take,including prescription and over-the-counter medicines, vitamins, and herbal supplements. SEPHIENCE and other medicines may affect each other causing side effects. SEPHIENCE may affect the way other medicines work, and other medicines may affect how SEPHIENCE works. Especially tell your healthcare provider if you take:

- a medicine that contains levodopa
- an antifolate medicine
- another medicine also used to lower Phe
- medicines used to treat erectile dysfunction (phosphodiesterase 5 inhibitors or PDE5)

Know the medicines you take. Keep a list of them with you to show your healthcare provider and pharmacist when you get a new medicine.

How should I take or give SEPHIENCE?

- Take or give SEPHIENCE exactly as your healthcare provider tells you. Your healthcare provider will tell you how much SEPHIENCE to take or give.
- Your healthcare provider may change your or your child’s dose of SEPHIENCE depending on your weight and age.
- Take or give SEPHIENCE 1 time each day with food. You must take or give more food after SEPHIENCE dose.
- SEPHIENCE comes as a packet containing oral powder.
  - For SEPHIENCE doses less than1,000 mg: mix SEPHIENCE oral powder with water or apple juice before taking or giving.
  - For SEPHIENCE doses 1,000 mg or greaterSEPHIENCE oral powder can be mixed with water, apple juice, strawberry jam or applesauce before taking or giving.
  - See the detailed Instructions for Usethat comes with SEPHIENCE for information about the correct way to prepare, take, or give a dose of SEPHIENCE oral powder.
- If you or your child miss a dose of SEPHIENCE, take or give it as soon as possible. Do not take 2 doses in a day. Continue with your normal dosing schedule the following day.
- During treatment with SEPHIENCE, you or your child will have regular check-ups with your healthcare provider.
- Your healthcare provider will do blood tests before and during your treatment with SEPHIENCE to check your blood Phe levels.
- Your healthcare provider may change your dose, temporarily stop, or permanently stop treatment with SEPHIENCE if you have certain side effects
- Your healthcare provider may change your diet during treatment. Follow your healthcare provider’s instructions and do not make any changes to your diet without first talking to your healthcare provider.

What are the possible side effects of SEPHIENCE?

SEPHIENCE may cause serious side effects including:

- increased bleeding problems.SEPHIENCE may increase your risk of bleeding. Tell your healthcare provider if you develop any symptoms of bleeding including:
  - bruising or red or purple skin marks
  - bleeding longer than usual or that does not stop
  - menstrual bleeding that is heavier than normal
- low blood Phe (hypophenylalaninemia).Low blood Phe levels is common during treatment with SEPHIENCE and can be severe.

The most common side effects of SEPHIENCE include:diarrhea, headache, stomach (abdominal) pain, yellow or orange stool (feces), and throat pain.

Tell your healthcare provider if you have any side effect that bothers you or that does not go away.

These are not all of the possible side effects of SEPHIENCE.

Call your healthcare provider for medical advice about side effects. You may report side effects to FDA at 1-800-FDA-1088.

You may also report side effects to PTC Therapeutics, Inc. at 1-866-562-4620 or email at usmedinfo@ptcbio.com.

How should I store SEPHIENCE?

- Store SEPHIENCE oral powder packets at room temperature between 68°F to 77°F (20°C to 25°C).
- For SEPHIENCE oral powder that is mixed with water, apple juice, strawberry jam, or applesauce:
  - If the SEPHIENCE mixture is not taken or given right away, cover and store the mixture at room temperature between 68°F to 77°F (20°C to 25°C) for up to 6 hours or refrigerate between 36°F to 46°F (2°C to 8°C) for no more than 24 hours.
    - If the stored SEPHIENCE mixture was prepared with water or apple juice,stir the mixture for 30 seconds or more before taking or giving the dose.
    - If the stored SEPHIENCE mixture was prepared with strawberry jam or applesauce,stir the mixture for 60 seconds or more before taking or giving the dose.
  - Throw away (discard) unused SEPHIENCE mixture after 6 hours at room temperature or after 24 hours if refrigerated.

Keep SEPHIENCE and all medicines out of the reach of children.

General information about the safe and effective use of SEPHIENCE.

Medicines are sometimes prescribed for purposes other than those listed in a Patient Information leaflet. Do not use SEPHIENCE for a condition for which it was not prescribed. Do not give SEPHIENCE to other people, even if they have the same symptoms that you have. It may harm them. You can ask your pharmacist or healthcare provider for information about SEPHIENCE that is written for health professionals.

What are the ingredients in SEPHIENCE?

Active ingredients: sepiapterin

Inactive ingredients: colloidal silicon dioxide, croscarmellose sodium, isomalt, magnesium stearate, mannitol,
microcrystalline cellulose, sucralose, and xanthan gum.

Manufactured by: Allphamed PHARBIL Arzneimittel GmbH
Hildebrand str. 12,
37081 Gottingen,
Germany (DEU)
Manufactured for:
PTC Therapeutics, Inc.
Warren, NJ 07059
SEPHIENCE is a registered trademark of PTC Therapeutics, Inc.
©2025 PTC Therapeutics, Inc. All rights reserved.
For more information, go to www.sephience.comor call 1-844-478-2227.

This Patient Information has been approved by the U.S. Food and Drug Administration.

Issued: 07/2025

INSTRUCTIONS FOR USE

SEPHIENCE (seh-FIGH-ence)
(sepiapterin)
oral powder

This Instructions for Use contains information on how to prepare, take, or give SEPHIENCE.

Ask your healthcare provider or pharmacist if you have any questions on how to prepare, take, or give SEPHIENCE.

The preparation steps differ based on the prescribed dose. Follow the steps specific to the dose your healthcare provider has prescribed. See the section called:

- SEPHIENCE Doses Less Than 1,000 mg or
- Instructions for SEPHIENCE Doses 1,000 mg or Greater

Each SEPHIENCE carton contains:

- 30 SEPHIENCE 250 mg dose packets or
- 30 SEPHIENCE 1,000 mg dose packets

Important Information you need to know before taking or giving SEPHIENCE:

- SEPHIENCE comes as a packet containing powder.
- Take or give SEPHIENCE exactly as your healthcare provider tells you.
- Be sure that you know what dose of SEPHIENCE your healthcare provider has prescribed. Your healthcare provider will prescribe SEPHIENCE 250 mg packet(s), SEPHIENCE 1,000 mg packet(s), or both types of packets to prepare your dose.
- Your healthcare provider may change your dose of SEPHIENCE depending on how you respond to treatment and based on your weight and age.
- Take or give SEPHIENCE 1 time each day with food. You must take or give more food after each SEPHIENCE dose.
- Do notuse SEPHIENCE oral powder packet(s) after the expiration date on the powder packet(s) and box. The expiration date is the last day of the expiration month.
- For SEPHIENCE doses less than 1,000 mg:SEPHIENCE oral powder is to be mixed with water or apple juice before taking or giving. Follow the section called Instructions for SEPHIENCE doses less than 1,000 mg.
- For SEPHIENCE doses 1,000 mg or greater:SEPHIENCE oral powder can be mixed with water, apple juice, strawberry jam, or applesauce before taking or giving. Follow the section called Instructions for SEPHIENCE Doses 1,000 mg or Greater.

Storing SEPHIENCE:

- Store SEPHIENCE oral powder packet(s) at room temperature between 68°F to 77°F (20°C to 25°C).
- For SEPHIENCE oral powder that is mixed with water, apple juice, strawberry jam, or applesauce:
  - If the SEPHIENCE mixture is not taken or given right away, cover and store the mixture at room temperature between 68°F to 77°F (20°C to 25°C) for up to 6 hours or in the refrigerator between 36°F to 46°F (2°C to 8°C) for up to 24 hours.
    - If the stored SEPHIENCE mixture was prepared with water or apple juice, stir the mixture for 30 seconds or more before taking or giving the dose.
    - If the stored SEPHIENCE mixture was prepared with strawberry jam or applesauce, stir the mixture for 60 seconds or more before taking or giving the dose.
  - Throw away (discard) unusedSEPHIENCE mixture after 6 hours at room temperature or after 24 hours if refrigerated. See Throwing away (disposing of) SEPHIENCE.

Keep SEPHIENCE and all medicines out of the reach of children.

Preparing to mix SEPHIENCE oral powder:

Instructions for SEPHIENCE Doses Less Than 1,000 mg:

- Your healthcare provider or pharmacist will tell you the amount of:
  - Water or apple juice needed to mix 1 dose of SEPHIENCE.
  - SEPHIENCE mixture (after mixed with water or apple juice) to give in milliliters (mL).
  - You may need to measure a smaller amount of mixture than you prepared to take or give the correct prescribed dose of SEPHIENCE.

Supplies needed to mix and give SEPHIENCE doses less than 1,000 mg (see Figure A):

- The number of SEPHIENCE 250 mg oral powder packet(s) needed for 1 dose, or one SEPHIENCE 1,000 mg packet(s)

Supplies not included with the SEPHIENCE oral powder packet carton(s):

- 1 small cup of water or apple juice
- 1 container for mixing
- 1 small spoon
- a 10 mL oral dosing syringe or recommended oral dosing syringe
- scissors (optional)

Ask your pharmacist for a container for mixing SEPHIENCE and an oral dosing syringe if you do not have these supplies.

Step 1:Find a clean, flat work surface. Place the following items on your clean, flat work surface:

- prescribed number of SEPHIENCE oral powder packets for your daily dose
- a small cup of water orapple juice
- container for mixing
- small spoon
- oral dosing syringe

Step 2:Check the label on the SEPHIENCE oral powder packet(s) to make sure you have the number of packets for the prescribed dose. Open the SEPHIENCE oral powder packet(s) by folding and tearing at the tear notch, or using scissors to cut the packet(s) open at the dotted line. Empty the entire contents of eachSEPHIENCE oral powder packet(s) into the container for mixing (see Figure B).

Step 3:Place the tip of the oral dosing syringe into the cup containing the water or apple juice. Pull back on the plunger and draw up the amount of water or apple juice needed to prepare the packet(s) for the prescribed dose.

Use 9 mL of water or apple juice for each 250 mg packet.For example:

- If you are preparing 1 packet of SEPHIENCE, you will need to add 9 mL of water or apple juice.
- If you are preparing 2 packets of SEPHIENCE, you will need to add 18 mL of water or apple juice.
- If you are preparing 3 packets of SEPHIENCE, you will need to add 27 mL of water or apple juice.
- If you are preparing 4 packets of SEPHIENCE, you will need to add 36 mL of water or apple juice.

If you are using one 1,000 mg packet to prepare the prescribed dose, you will need to add 36 mL of water or apple juice.

Slowly add the water or apple juice to the container for mixing containing the SEPHIENCE oral powder. Repeat until the entire amount of water or apple juice that is needed to mix the number of SEPHIENCE oral powder packets has been added to the container for mixing (see Figure C).

Step 4:Stir the SEPHIENCE oral powder mixed with water or apple juice well for 30 seconds or more with a small spoon until the SEPHIENCE mixture is free of lumps (see Figure D).

SEPHIENCE oral powder is not expected to dissolve completely. This is normal.

Step 5:Place the tip of the oral dosing syringe into the mixture inside the container used for mixing. Pull back on the plunger until the edge of the plunger lines up with the marking for the dose as instructed by your healthcare provider in mL (milliliters) (see Figure E).

Step 6:Take the oral dosing syringe out of the container used for mixing. Carefully turn the oral dosing syringe so that the tip is pointing up. Check the syringe marking to make sure that the amount of SEPHIENCE mixture in the oral dosing syringe lines up with the prescribed SEPHIENCE dose in mL (milliliters) (see Figure F).

Your dose may be different than the dose shown in Figure F.

Give SEPHIENCE mixture right away after it is drawn up into the syringe.

Step 7:Place the tip of the oral dosing syringe into your child’s mouth. Point the tip of the oral dosing syringe toward either cheek (see Figure G).

Push on the plunger slowly, until all the mixture in the oral dosing syringe is given.

If the prescribed dose is more than 10 mL, repeatStep 5 to Step 7 until you give the total amount of prescribed dose in mL (milliliters)by your healthcare provider.

Step 8:If there is any mixture left in the oral dosing syringe, draw up more water or apple juice into the oral dosing syringe and give until no mixture is left in the oral dosing syringe.

Step 9:Throw away any SEPHIENCE mixture remaining in the container used for mixing in the household trash.

See Throwing away (disposing of) SEPHIENCE. Remove the plunger from the barrel of the oral dosing syringe. Wash the oral dosing syringe and container used for mixing with warm water and air dry. When the oral dosing syringe is dry, put the plunger back into the barrel. Store the oral dosing syringe and container used for mixing for the next use.

Instructions for SEPHIENCE Doses 1,000 mg or Greater:

Supplies needed to mix and take or give SEPHIENCE doses 1,000 mg or greater (see Figure A):

- The number of SEPHIENCE 250 mg packet(s) or SEPHIENCE 1,000 mg packet(s) needed for 1 dose

Supplies not included with the SEPHIENCE oral powder packet carton(s):

- a small cup of water, apple juice, strawberry jam, orapplesauce
- 1 tablespoon to measure the water, apple juice, strawberry jam, orapplesauce
- additional small cup of water orapple juice to rinse the cup
- 1 container for mixing
- scissors (optional)

- Your healthcare provider will tell you the number of packets, and the amount of water, apple juice, strawberry jam, or applesauce needed to mix 1 dose of SEPHIENCE per Table 1below.

Table 1: Number of SEPHIENCE Packets to Prepare a SEPHIENCE Mixture for Doses of 1,000 mg or Greater
Find your prescribed number of packets: |  | Choose one of the following:; - Water - Apple juice - Strawberry jam - Applesauce
Number of 1,000 mg packets | Number of 250 mg packets | Amount of water, apple juice, strawberry jam, orapplesauce to mix the packet(s)
1 | 0 | 2 Tbsp or 30 mL
1 | 1 | 4 Tbsp or 60 mL
1 | 2 | 4 Tbsp or 60 mL
1 | 3 | 4 Tbsp or 60 mL
2 | 0 | 4 Tbsp or 60 mL
2 | 1 | 6 Tbsp or 90 mL
2 | 2 | 6 Tbsp or 90 mL
2 | 3 | 6 Tbsp or 90 mL
3 | 0 | 6 Tbsp or 90 mL
3 | 1 | 8 Tbsp or 120 mL
3 | 2 | 8 Tbsp or 120 mL
3 | 3 | 8 Tbsp or 120 mL
4 | 0 | 8 Tbsp or 120 mL
4 | 1 | 10 Tbsp or 150 mL
4 | 2 | 10 Tbsp or 150 mL
4 | 3 | 10 Tbsp or 150 mL
5 | 0 | 10 Tbsp or 150 mL
5 | 1 | 12 Tbsp or 180 mL
5 | 2 | 12 Tbsp or 180 mL
5 | 3 | 12 Tbsp or 180 mL
6 | 0 | 12 Tbsp or 180 mL

Ask your pharmacist for a container for mixing SEPHIENCE if you do not have these supplies.

Step 1:Find a clean, flat work surface. Place the following items on your clean, flat work surface:

- prescribed number of SEPHIENCE oral powder packets
- a small cup of water, apple juice, strawberry jam, orapplesauce
- additional small cup of water orapple juice to rinse the cup (see Step 6below)
- tablespoon
- container for mixing

Step 2:Check the label on the SEPHIENCE oral powder packet(s) to make sure you have the number of packets for the prescribed dose. Open the SEPHIENCE oral powder packet(s) by folding and tearing at the tear notch or using scissors to cut the packet(s) open at the dotted line. Empty the entire contents of eachSEPHIENCE oral powder packet(s) into the container for mixing (see Figure B).

Step 3:Mix the SEPHIENCE oral powder packet(s) with water, apple juice, strawberry jam, orapplesauce. See Table 1above.

Slowly add the water, apple juice, strawberry jam, orapplesauce to the container for mixing containing the SEPHIENCE oral powder. Repeat until the entire amount of water, apple juice, strawberry jam, orapplesauce that is needed to mix the number of SEPHIENCE oral powder packets has been added to the container for mixing (see Figure C).

Step 4:If you used water or apple juice to mix the SEPHIENCE oral powder packet(s), stir the mixture well for 30 seconds or more with the tablespoon until the SEPHIENCE mixture is free of lumps (see Figure D).

SEPHIENCE oral powder is not expected to dissolve completely.
or

If you used strawberry jam or applesauce to mix the SEPHIENCE oral powder packet(s), stir the mixture well for 60 seconds or more with the tablespoon.

Step 5:Give or take all of the SEPHIENCE mixture from the container used for mixing.

Step 6:If any SEPHIENCE mixture remains in the container used for mixing, rinse the container with water or apple juice (at least 15 mL). Swallow the rinse right away. Repeat this step until no mixture remains in the container used for mixing.

Step 7:Wash the container used for mixing with warm water and air dry. Store the container used for mixing for the next use.

Throwing away (disposing of) SEPHIENCE:

- Ask your pharmacist how to properly throw away (dispose of) SEPHIENCE oral powder packet(s) that are not needed or that have expired.

Manufactured by:
Allphamed PHARBIL Arzneimittel GmbH
Hildebrand str. 12,
37081 Gottingen,
Germany (DEU)
Manufactured for:
PTC Therapeutics, Inc.
Warren, NJ 07059
This Instructions for Use has been approved by the U.S. Food and Drug Administration.
Approved: 07/2025